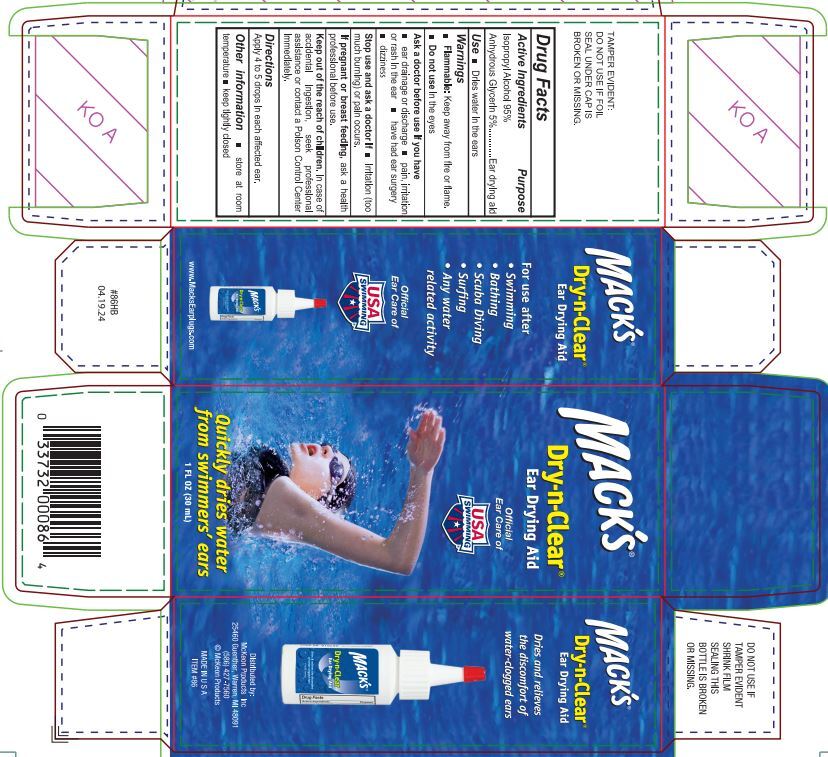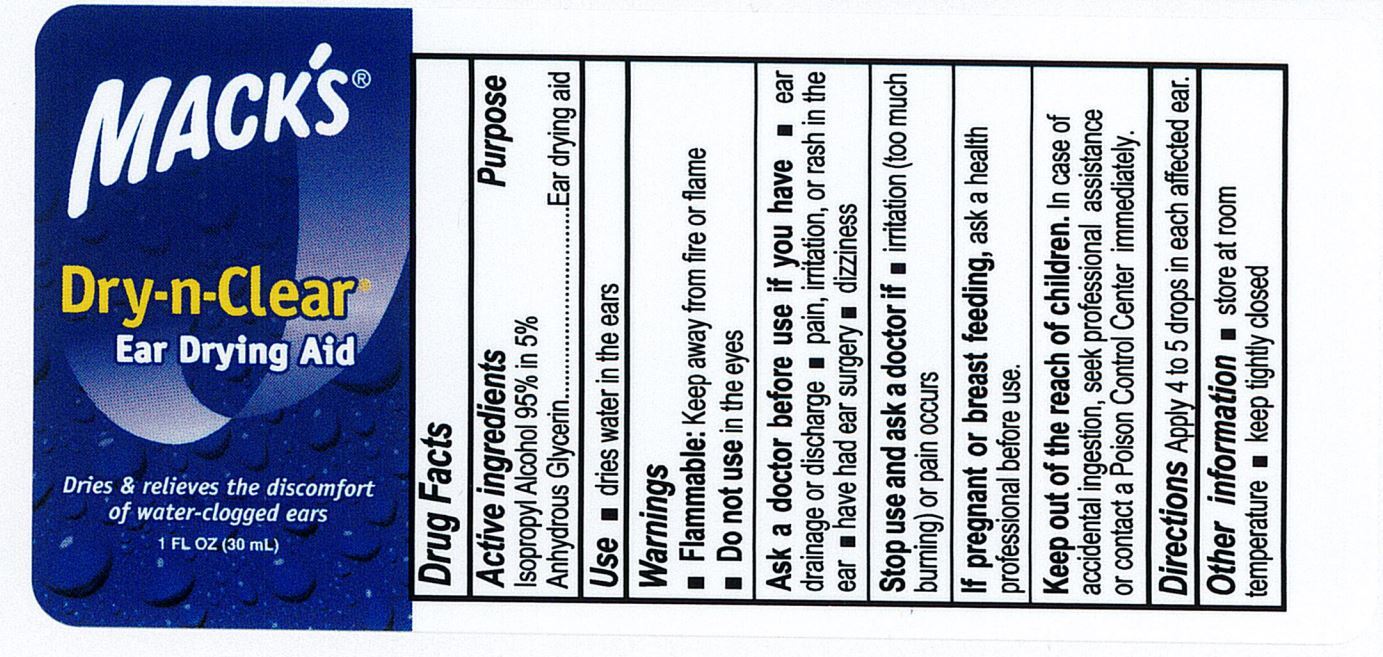 DRUG LABEL: Macks Dry n Clear
NDC: 66354-001 | Form: LIQUID
Manufacturer: McKeon Products Inc
Category: otc | Type: HUMAN OTC DRUG LABEL
Date: 20240801

ACTIVE INGREDIENTS: ISOPROPYL ALCOHOL 950 mg/1 mL
INACTIVE INGREDIENTS: GLYCERIN

Mack’s Dry-n-Clear

Active Ingredient

Isopropyl Alcohol 95% in anhydrous glycerin

Purpose

Ear drying aid

Use

Dries water in the ears.

Warnings

Flammable: Keep away from fire and flame.

Do not use

in the eyes.

Ask a doctor before use if you have

Ear drainage or discharge.

Pain, irritation, or rash in the ear.

Have had ear surgery.

Dizziness.

Stop use and ask doctor if

Irritation (too much burning) or pain occurs.

If pregnant or breast feeding,

ask a health professional before use.

Keep out of reach of children.

- In case of accidental ingestion, seek professional assistant or contact a Poison Control Center immediately.

Directions

Apply 4 to 5 drops in each affected ear..

Other information

Store at room temperature. Keep tightly closed

INACTIVE INGREDIENT

Glycerin